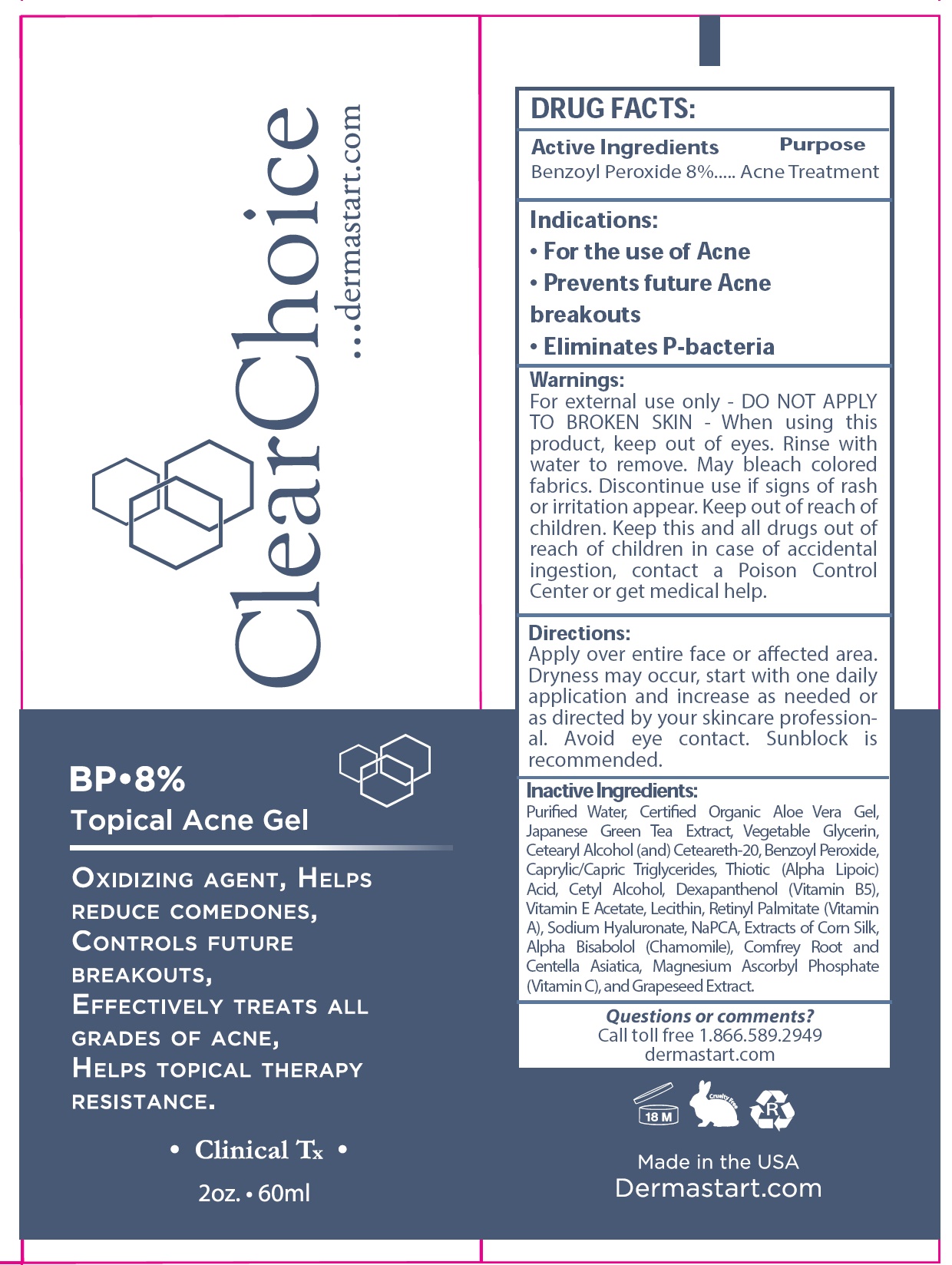 DRUG LABEL: Clear Choice BP 8 Topical Acne
NDC: 83722-001 | Form: GEL
Manufacturer: Dermastart Inc
Category: otc | Type: HUMAN OTC DRUG LABEL
Date: 20240207

ACTIVE INGREDIENTS: BENZOYL PEROXIDE 80 mg/1 mL
INACTIVE INGREDIENTS: WATER; ALOE VERA LEAF; GREEN TEA LEAF; CETOSTEARYL ALCOHOL; POLYOXYL 20 CETOSTEARYL ETHER; MEDIUM-CHAIN TRIGLYCERIDES; CETYL ALCOHOL; PANTOTHENIC ACID; .ALPHA.-TOCOPHEROL ACETATE; VITAMIN A; HYALURONATE SODIUM; CHAMOMILE; ASCORBIC ACID; VITIS VINIFERA SEED

Clear Choice BP 8% Topical Acne Gel

Active Ingredients

Benzoyl Peroxide 8%

Purpose

Acne Treatment

Indications:

- For the use of Acne
- Prevents future Acne breakouts
- Eliminates P-bacteria

Warnings:

For external use only - DO NOT APPLY TO BROKEN SKIN

- When using this product,

keep out of eyes. Rinse with water to remove. May bleach colored fabrics. Discontinue use if signs of rash or irritation appear.

Keep out of reach of children.

Keep this and all drugs out of reach of children in case of accidental ingestion, contact a Poison Control Center or get medical help.

Directions:

Apply over entire face or affected area. Dryness may occur, start with one daily application and increase as needed or as directed by your skincare professional. Avoid eye contact. Sunblock is recommended.

Inactive Ingredients:

Purified Water, Certified Organic Aloe Vera Gel, Japanese Green Tea Extract, Vegetable Glycerin, Cetearyl Alcohol (and) Ceteareth-20, Benzoyl Peroxide, Caprylic/Capric Triglycerides, Thiotic (Alpha Lipoic) Acid, Cetyl Alcohol, Dexapanthenol (Vitamin B5), Vitamin E Acetate, Lecithin, Retinyl Palmitate (Vitamin A), Sodium Hyaluronate, NaPCA, Extracts of Corn Silk, Alpha Bisabolol (Chamomile), Comfrey Root and Centella Asiatica, Magnesium Ascorbyl Phosphate (Vitamin C), and Grapeseed Extract.

Questions or comments?

Call toll free 1.866.589.2949

dermastart.com